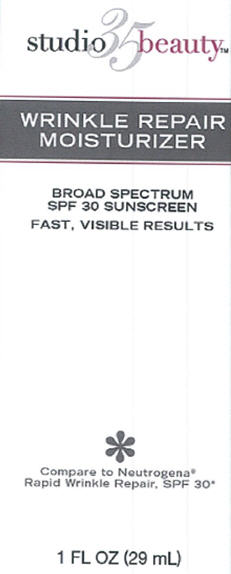 DRUG LABEL: Walgreens Wrinkle Repair Moisturizer SPF30
NDC: 0363-9362 | Form: CREAM
Manufacturer: Walgreens Company
Category: otc | Type: HUMAN OTC DRUG LABEL
Date: 20140110

ACTIVE INGREDIENTS: AVOBENZONE 2 g/100 mL; HOMOSALATE 4 g/100 mL; OCTISALATE 4 g/100 mL; OCTOCRYLENE 2 g/100 mL
INACTIVE INGREDIENTS: WATER; DECAMETHYLTETRASILOXANE; ISONONYL ISONONANOATE; CETYL ALCOHOL; GLYCERIN; STEARETH-21; STEARYL ALCOHOL; NYLON-12; SILICON DIOXIDE; GLYCERYL MONOSTEARATE; PEG-100 STEARATE; PHENOXYETHANOL; ETHYLHEXYLGLYCERIN; DIMETHICONE; DIMETHICONE/DIENE DIMETHICONE CROSSPOLYMER; AMMONIUM NONOXYNOL-4 SULFATE; PROPYLENE GLYCOL; MYRTUS COMMUNIS LEAF; XANTHAN GUM; VITAMIN A PALMITATE; POLYACRYLAMIDE (10000 MW); C13-14 ISOPARAFFIN; LAURETH-7; SODIUM HYDROXIDE; EDETATE DISODIUM; ASCORBIC ACID; POLYSORBATE 20; BUTYLATED HYDROXYTOLUENE; HYALURONIC ACID

studio 35 beauty™ Wrinkle Repair Moisturizer

Active ingredient

Avobenzone 2.0%
Homosalate 4.0%
Octisalate 4.0%
Octocrylene 2.0%

Purpose

Sunscreen

Uses

- helps prevent sunburn
- If used as directed with other sun protection measures (see Directions), decreases the risk of skin cancer and early skin aging caused by the sun

Warnings

For external use only.

Do not use on

- damaged or broken skin.

When using this product

- keep out of eyes. Rinse with water to remove.

Stop use and ask a doctor

- if rash occurs.

Keep Out of Reach of Children.

If swallowed, get medical help or contact a Poison Control Center right away.

Directions

- Apply liberally 15 minutes before sun exposure.
- Children under 6 months of age: ask a doctor
- Sun Protection Measures: Spending time in the sun increases your risk of skin cancer and early skin aging. To decrease this risk, regularly use a sunscreen with a Broad Spectrum SPF value of 15 or higher and other sun protection measures including:
  - limit time in the sun, especially from 10 a.m. - 2 p.m.
  - wear long-sleeved shirts, pants, hats and sunglasses

Other Information

- protect the product in this container from excessive heat and direct sun

Inactive ingredients

water, decamethyltetrasiloxane, isononyl isononanoate, cetyl alcohol, glycerin, steareth-21, stearyl alcohol, nylon-12, silica, glyceryl stearate, PEG-100 stearate, phenoxyethanol, ethylhexylglycerin, dimethicone, dimethicone/vinyldimethicone crosspolymer, sodium styrene/acrylates divinylbenzene copolymer, ammonium nonoxynol-4-sulfate, fragrance, propylene glycol, myrtus communis extract, xanthan gum, retinyl palmitate, polyacrylamide, C13-14 isoparaffin, laureth-7, sodium hydroxide, disodium EDTA, ascorbic acid, polysorbate 20, BHT, hyaluronic acid

Package/Label Principal Display Panel

studio 35 beauty™ Wrinkle Repair Moisturizer
Broad Spectrum SPF30 Sunscreen
Fast, Visible Results

Compare to Neutrogena®
Rapid Wrinkle Repair, SPF 30

1 Fl Oz (29 mL)

Distributed by: Walgreen Co.
200 Wilmot Rd., Deerfield, IL 60015
100% Satisfaction Guaranteed

walgreens.com ©2012 Walgreen Co.

Manufactured in Israel

Carton Label